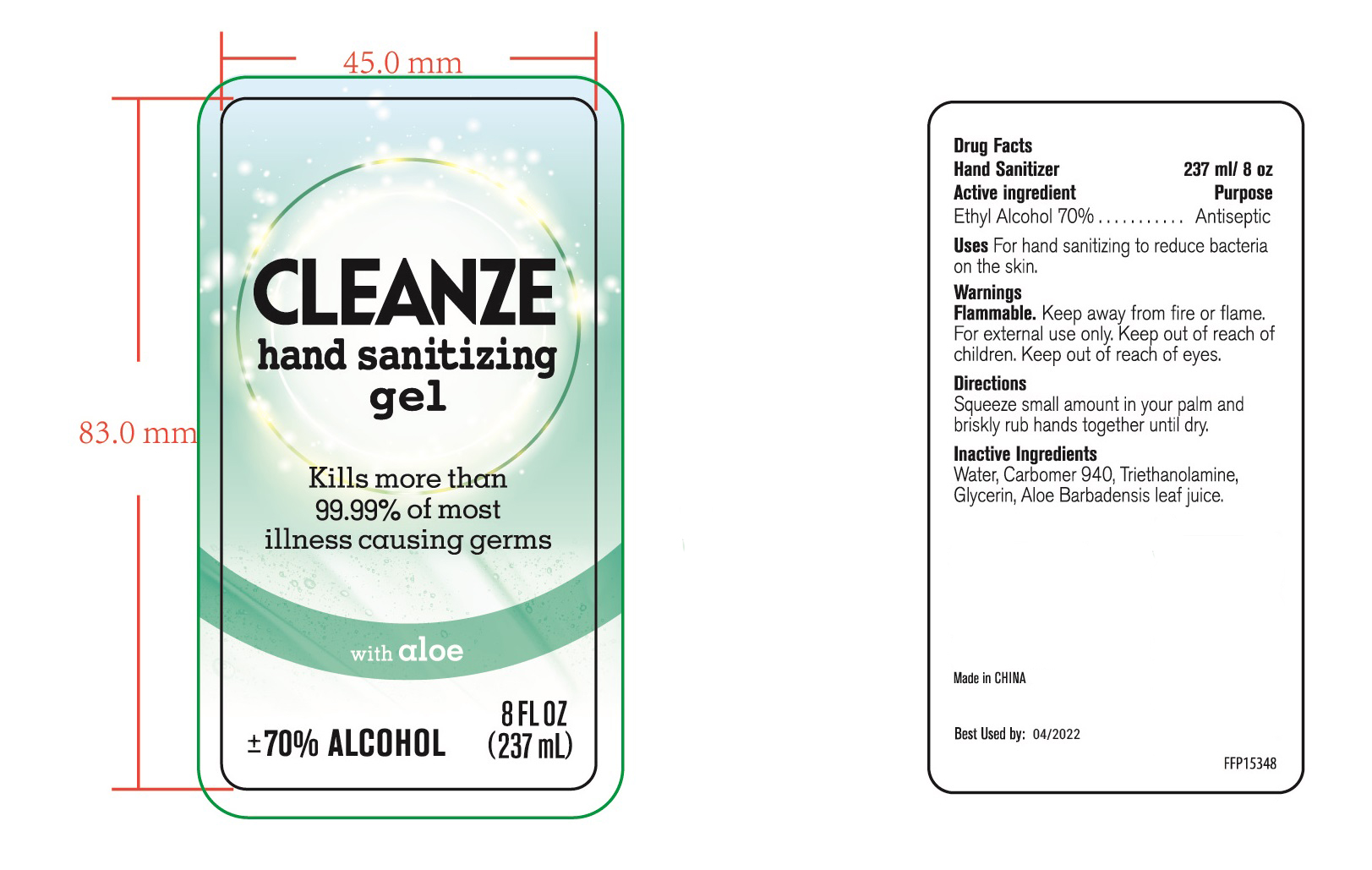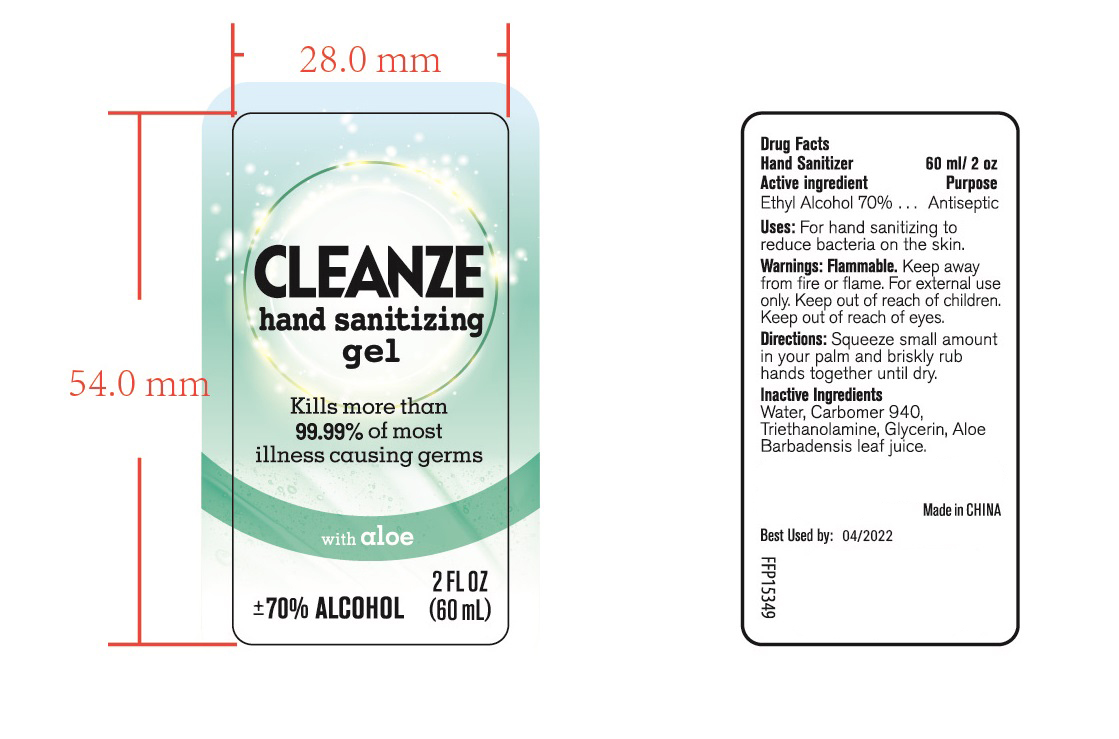 DRUG LABEL: HAND SANITIZER
NDC: 47993-246 | Form: GEL
Manufacturer: NINGBO JIANGBEI OCEAN STAR TRADING CO.,LTD
Category: otc | Type: HUMAN OTC DRUG LABEL
Date: 20201104

ACTIVE INGREDIENTS: ALCOHOL 70 g/112 mL
INACTIVE INGREDIENTS: WATER; CARBOMER 940 12 g/112 mL; GLYCERIN 2 g/112 mL; TRIETHANOLAMINE BENZOATE; ALOE VERA LEAF

47993-246

Active ingredients

Ethyl Alcohol 70%

PURPOSE

Antiseptic

Uses：

For hand sanitizing to readuce bacteria on the skin.

Warnings:

Flammable. Keep away from fire or flame. For external use only. Keep out of reach of children. Keep out of reach of eyes.

Keep out of reach of children.

Directions:

Squeeze small amount in your palm and briskly rub hands together until dry.

Inactive Ingredients:

Water,Carbomer 940,Triethanolamine,Glycerin,Aloe Barbadensis Leaf Juice